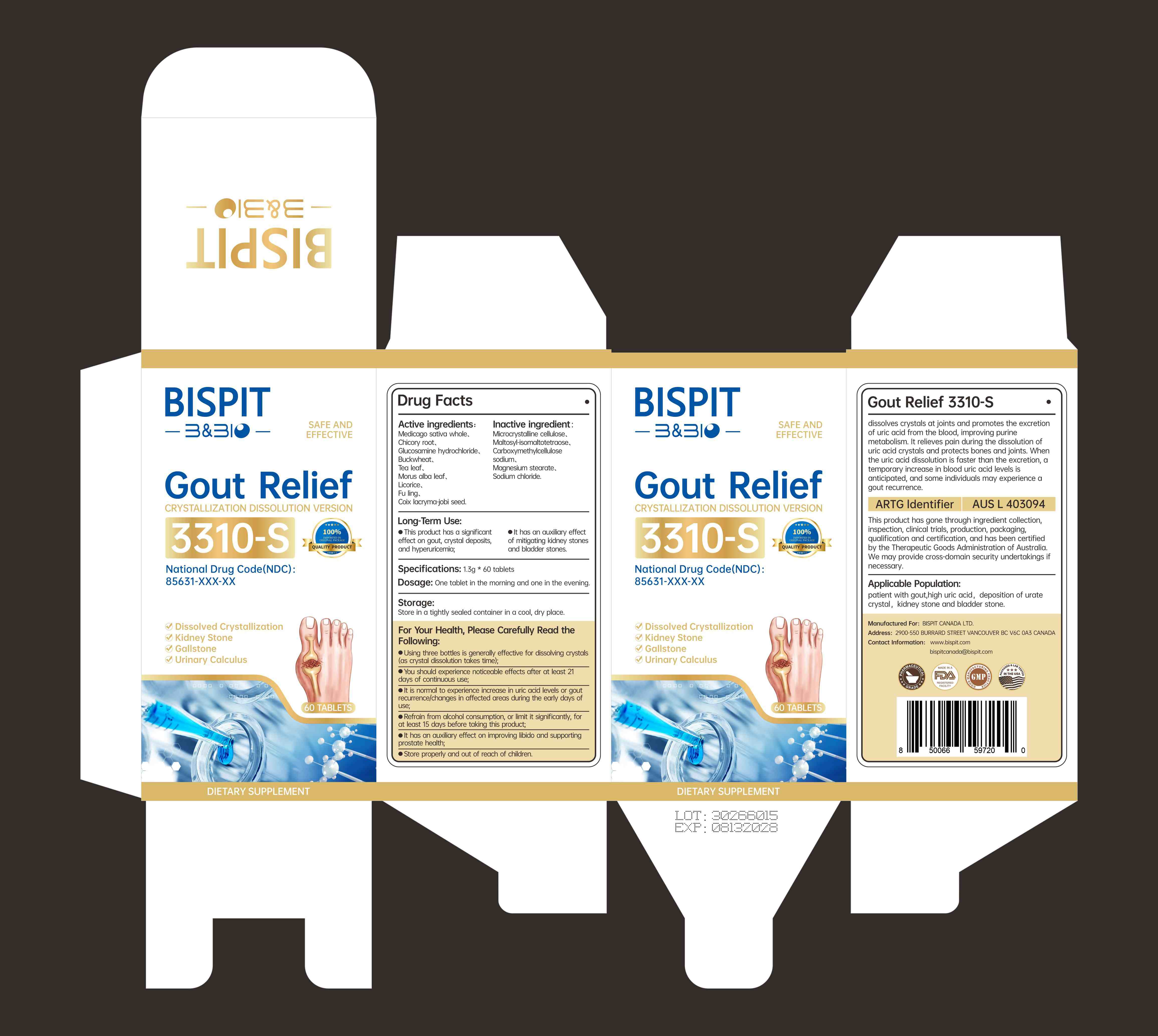 DRUG LABEL: Gout Relief 3310-S
NDC: 85631-006 | Form: CAPSULE
Manufacturer: Bispit Canada Ltd.
Category: homeopathic | Type: HUMAN OTC DRUG LABEL
Date: 20250901

ACTIVE INGREDIENTS: COIX LACRYMA-JOBI SEED 104 mg/1.3 g; MEDICAGO SATIVA WHOLE 260 mg/1.3 g; BUCKWHEAT 91 mg/1.3 g; TEA LEAF 65 mg/1.3 g; MORUS ALBA LEAF 169 mg/1.3 g; CHICORY ROOT 299 mg/1.3 g; FU LING 26 mg/1.3 g; GLUCOSAMINE HYDROCHLORIDE 130 mg/1.3 g; LICORICE 2.6 mg/1.3 g
INACTIVE INGREDIENTS: MALTOSYL-ISOMALTOTETRAOSE; SODIUM CHLORIDE; MAGNESIUM STEARATE; MICROCRYSTALLINE CELLULOSE; CARBOXYMETHYLCELLULOSE SODIUM

85631-006-01-Gout Relief 3310-S-NEW

ACTIVE INGREDIENT

MEDICAGO SATIVA WHOLE 20.00%
CHICORY ROOT 23.00%
GLUCOSAMINE HYDROCHLORIDE 10.00%
BUCKWHEAT 7.00%
TEA LEAF 5.00%
MORUS ALBA LEAF 13.00%
LICORICE 0.20%
FU LING 2.00%
COIX LACRYMA-JOBI SEED 8.00%

INACTIVE INGREDIENT

This product has a significanteffect on gout, crystal deposits,and hyperuricemia;
elt has an auxiliary effectof mitigating kidney stonesand bladder stones

Keep out of reach of children

DOSAGE AND ADMINISTRATION

The product has great somatosensation after taking it atleast 21 days in the earty stage;3. Elevated uric acid or gout recurrence and site changes arenoral in the earty stage of taking this product;

INDICATIONS AND USAGE

Dissolved CrystallizationKidney StoneGallstone< Urinary Calculus

Do not use if seal is broken.

Do not eat freshness packet enclosed.

Keep out of direct sunlight, high temperature, and humidity.

Store in a cool, dry place.

WARNINGS

For your health, please read the followingcarefully
1. The use of three vials can effectivety dissolve crystallization (ittakes time to dissolve crystallization);2. The product has great somatosensation after taking it atleast 21 days in the early stage;3. Elevated uric acid or gout recurrence and site changes arenormal in the early stage of taking this product;4. Try not to drink alcohol or drink less 15 days before takingthis product;
5. This product certainly has significant effect on gout,crystallization and hyperuricemia;

PURPOSE

This product has a significanteffect on gout, crystal deposits,and hyperuricemia; elt has an auxiliary effectof mitigating kidney stonesand bladder stones